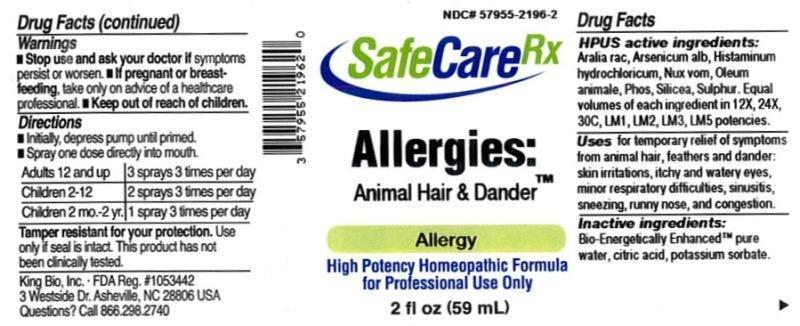 DRUG LABEL: Allergies Animal Hair and Dander
NDC: 57955-2196 | Form: LIQUID
Manufacturer: King Bio Inc.
Category: homeopathic | Type: HUMAN OTC DRUG LABEL
Date: 20150728

ACTIVE INGREDIENTS: ARALIA RACEMOSA ROOT 12 [hp_X]/59 mL; ARSENIC TRIOXIDE 12 [hp_X]/59 mL; HISTAMINE DIHYDROCHLORIDE 12 [hp_X]/59 mL; STRYCHNOS NUX-VOMICA SEED 12 [hp_X]/59 mL; CERVUS ELAPHUS HORN OIL 12 [hp_X]/59 mL; PHOSPHORUS 12 [hp_X]/59 mL; SILICON DIOXIDE 12 [hp_X]/59 mL; SULFUR 12 [hp_X]/59 mL
INACTIVE INGREDIENTS: WATER; ANHYDROUS CITRIC ACID; POTASSIUM SORBATE

Allergies: Animal Hair and Dander

ACTIVE INGREDIENT

Drug Facts__________________________________________________________________________________________________________

HPUS active ingredients: Aralia racemosa, Arsenicum album, Histaminum hydrochloricum, Nux vomica, Oleum animale, Phosphorus, Silicea, Sulphur. Equal volumes of each ingredient in 12X, 24X, 30C, LM1, LM2, LM3, LM5 potencies.

INDICATIONS AND USAGE

Uses for temporary relief of symptoms from animal hair, feathers and dander: skin irritations, itchy and watery eyes, minor respiratory difficulties, sinusitis, sneezing, runny nose, and congestion.

INACTIVE INGREDIENT

Inactive Ingredients: Bio-Energetically Enhanced™ pure water, citric acid and potassium sorbate.

Warnings

- Stop use and ask your doctor if symptoms persist or worsen.
- If pregnant or breast-feeding, take only on advice of a healthcare professional.

- Keep out of reach of children.

Directions

- Initially, depress pump until primed.
- Spray one dose directly into mouth.
- Adults 12 and up: 3 sprays 3 times per day.
- Children 2-12: 2 sprays 3 times per day.
- Children 2 mo-2yr: 1 sprary 3 times per day.

OTHER SAFETY INFORMATION

Tamper resistant for your protection. Use only if seal is intact. This product has not been clinically tested.

PURPOSE

Uses for temporary relief of symptoms from animal hair, feathers and dander:

- skin irritations
- itchy and watery eyes
- minor respiratory difficulties
- sinusitis
- sneezing
- runny nose
- congestion